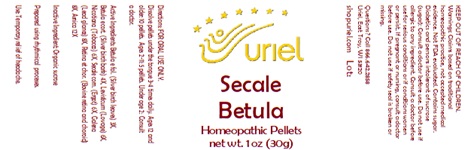 DRUG LABEL: Secale Betula
NDC: 48951-8175 | Form: PELLET
Manufacturer: Uriel Pharmacy Inc.
Category: homeopathic | Type: HUMAN OTC DRUG LABEL
Date: 20241125

ACTIVE INGREDIENTS: BETULA PUBESCENS LEAF 3 [hp_X]/1 1; BETULA PUBESCENS BARK 4 [hp_X]/1 1; LEVISTICUM OFFICINALE ROOT 6 [hp_X]/1 1; TOBACCO LEAF 6 [hp_X]/1 1; CLAVICEPS PURPUREA SCLEROTIUM 6 [hp_X]/1 1; LEAD SULFIDE 8 [hp_X]/1 1; BOS TAURUS EYE 8 [hp_X]/1 1; ARNICA MONTANA 12 [hp_X]/1 1
INACTIVE INGREDIENTS: SUCROSE

Secale Betula

INDICATIONS AND USAGE

Directions: FOR ORAL USE ONLY.

DOSAGE AND ADMINISTRATION

Dissolve pellets under the tongue 3-4 times daily. Ages 12 and older: 10 pellets. Ages 2-11: 5 pellets. Under age 2: Consult a doctor.

ACTIVE INGREDIENT

Active Ingredients: Betula e fol. (Silver birch leaves) 3X, Betula e cort. (Silver birch bark) 4X, Levisticum (Lovage) 6X, Nicotiana (Tobacco) 6X, Secale corn. (Ergot) 6X, Galena (Lead glance) 8X, Retina et chor. (Bovine retina and choroid) 8X, Arnica 12X

Inactive Ingredient: Organic sucrose

Prepared using rhythmical processes.

PURPOSE

Use: Temporary relief of headache.

KEEP OUT OF REACH OF CHILDREN.

WARNINGS

Warnings: Claims based on traditional homeopathic practice, not accepted medical evidence. Not FDA evaluated. Contains sugar. Diabetics and persons intolerant of sucrose (sugar): Consult a doctor before use. Do not use if allergic to any ingredient. Consult a doctor before use for serious conditions or if conditions worsen or persist. If pregnant or nursing, consult a doctor before use. Do not use if safety seal is broken or missing.

QUESTIONS

Questions? Call 866.642.2858 Uriel, East Troy, WI 53120 shopuriel.com Lot: